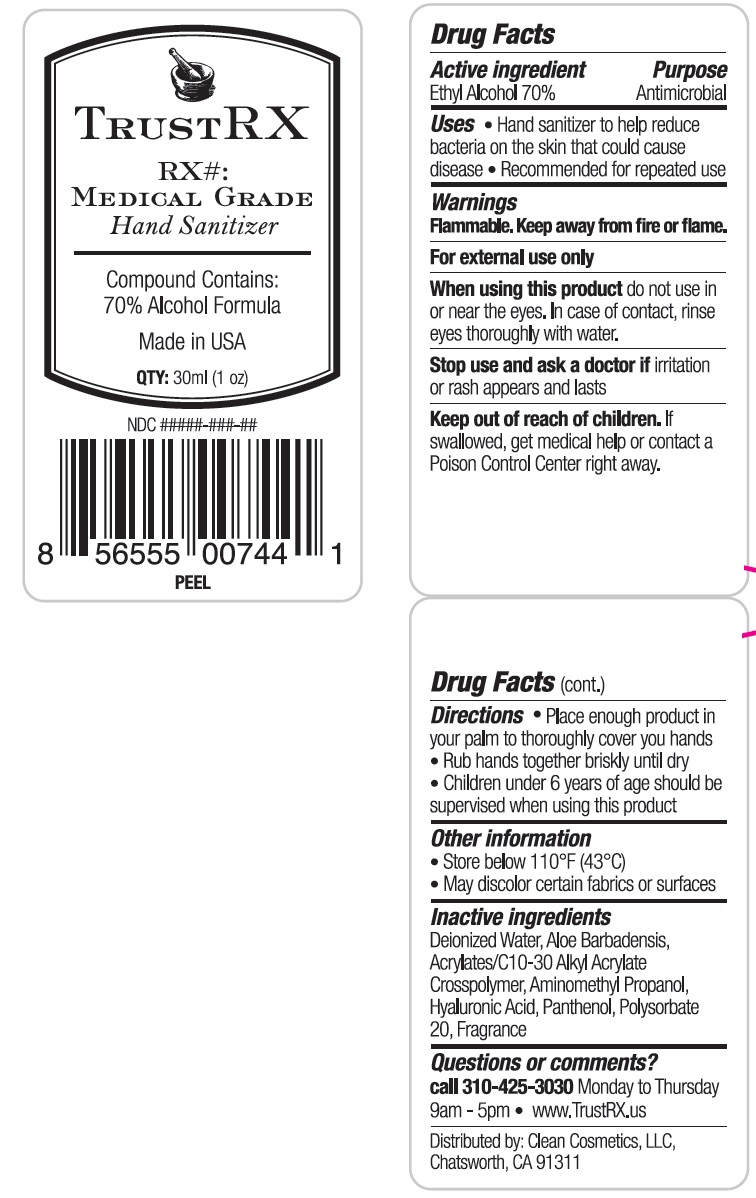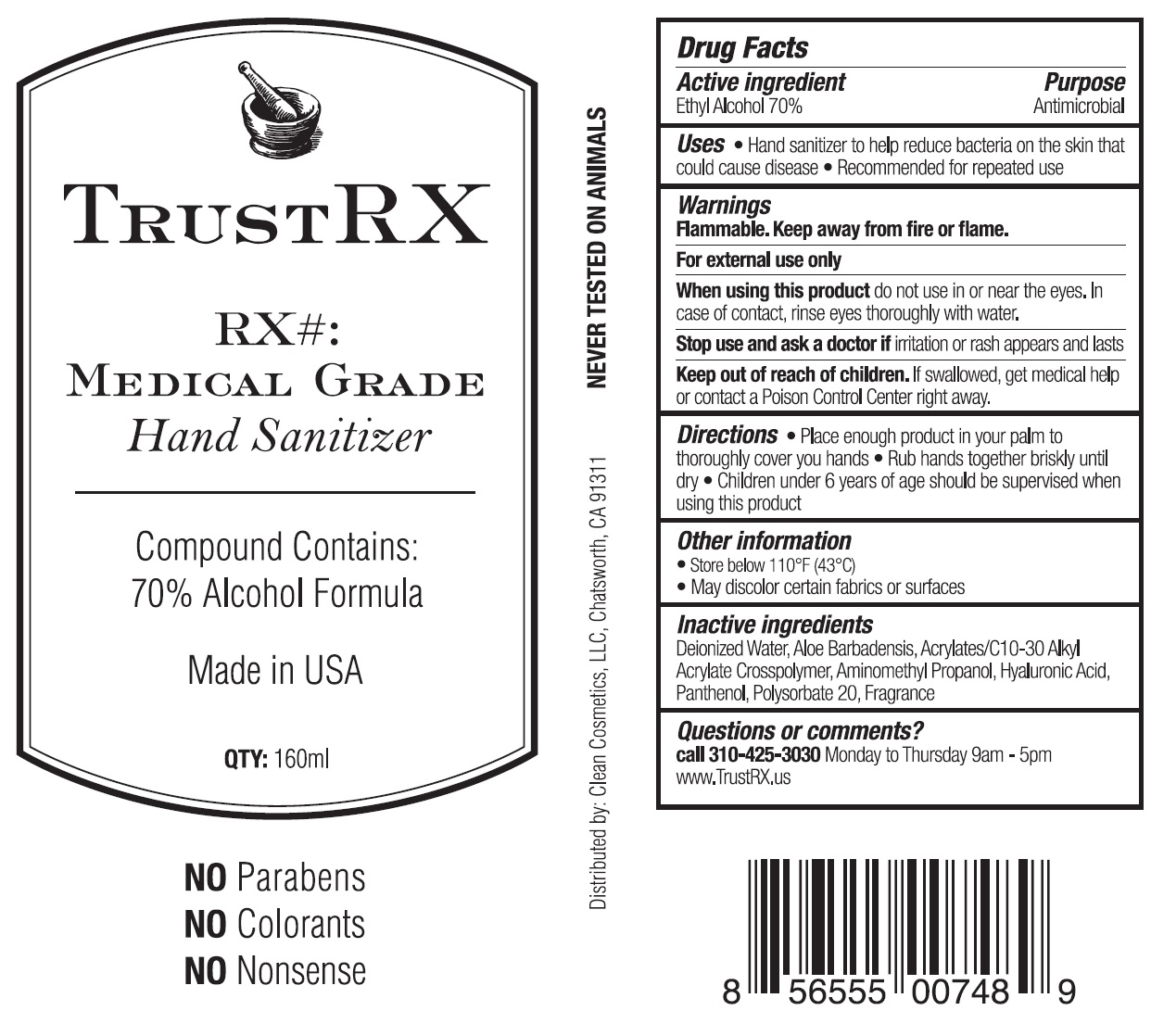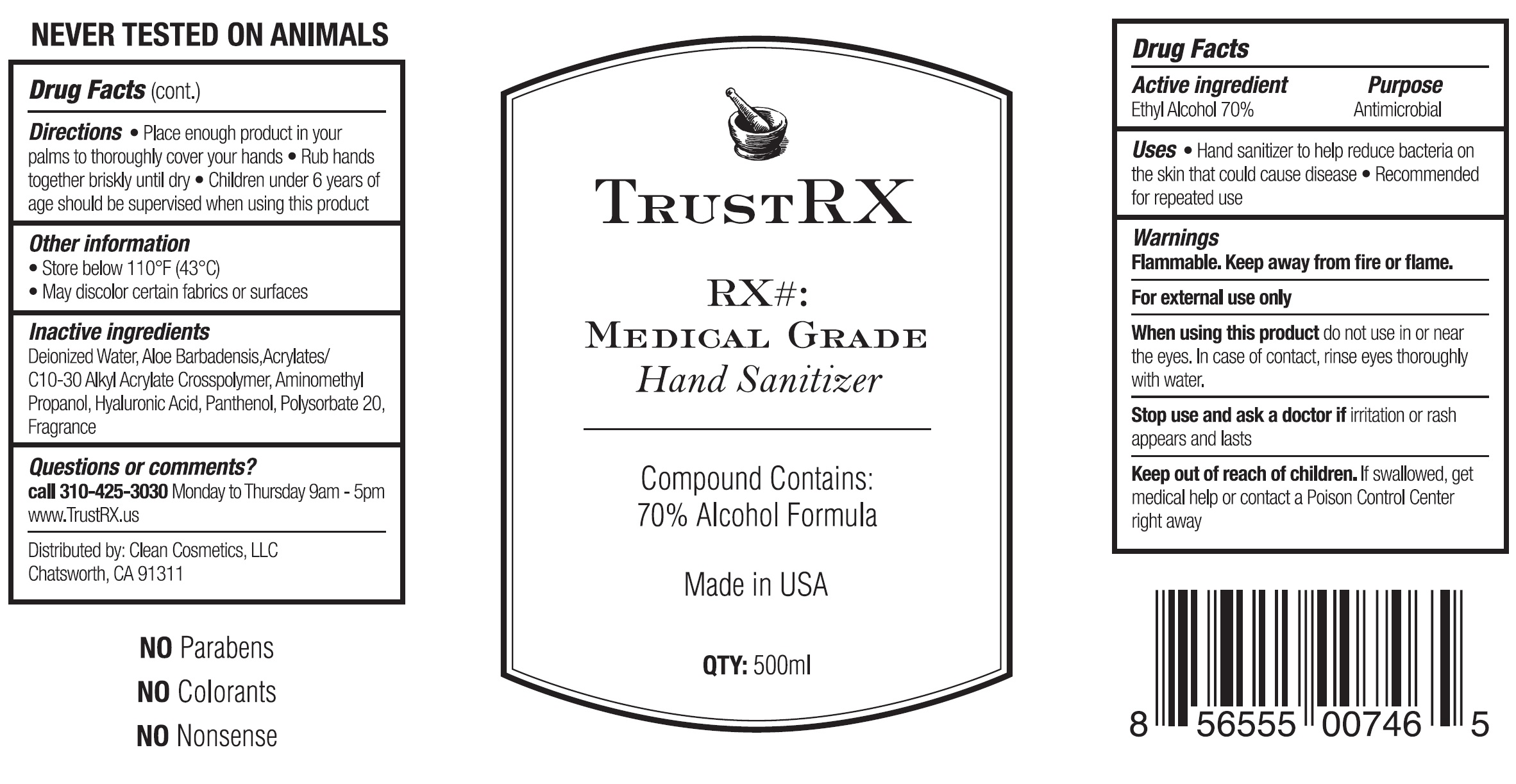 DRUG LABEL: TrustRX Hand Sanitizer
NDC: 80843-001 | Form: LIQUID
Manufacturer: Clean Cosmetics, LLC
Category: otc | Type: HUMAN OTC DRUG LABEL
Date: 20201015

ACTIVE INGREDIENTS: ALCOHOL 0.7 mL/1 mL
INACTIVE INGREDIENTS: WATER; ALOE VERA LEAF; CARBOMER INTERPOLYMER TYPE A (ALLYL SUCROSE CROSSLINKED); AMINOMETHYLPROPANOL; HYALURONIC ACID; PANTHENOL; POLYSORBATE 20

TrustRX Hand Sanitizer

Active ingredient

Ethyl Alcohol 70%

Purpose

Antimicrobial

Uses

- Hand Sanitizer to help reduce bacteria on the skin that could cause disease.
- Recommende for repeated use.

Warnings

Flammable. Keep away from fire or flame.

For external use only

When using this product

do not use in or near eyes. In case of contact, rinse thoroughly with water.

Stop use and ask a doctor if

irritation or rash appears and lasts

Keep out of reach of children.

If swallowed, get medical help or contact a Poison Control Center right away.

Directions

- Place enough product in your palm to thoroughly cover you hands
- Rub hands together briskly until dry.
- Children under 6 years of age should be supervised when using this product

Other information

- Store below 110°F (43°C)
- May discolor certain fabrics or surfaces

Inactive ingredients

Deionized Water, Aloe Barbadensis, Acrylates/C10-30 Alkyl Acrylate Crosspolymer, Aminomethyl Propanol, Hyaluronic Acid, Panthenol, Polysorbate 20, Fragrance

Questions or comments?

call 310-425-3030 Monday to Thursday 9am-5pm

- www.TrustRX.us